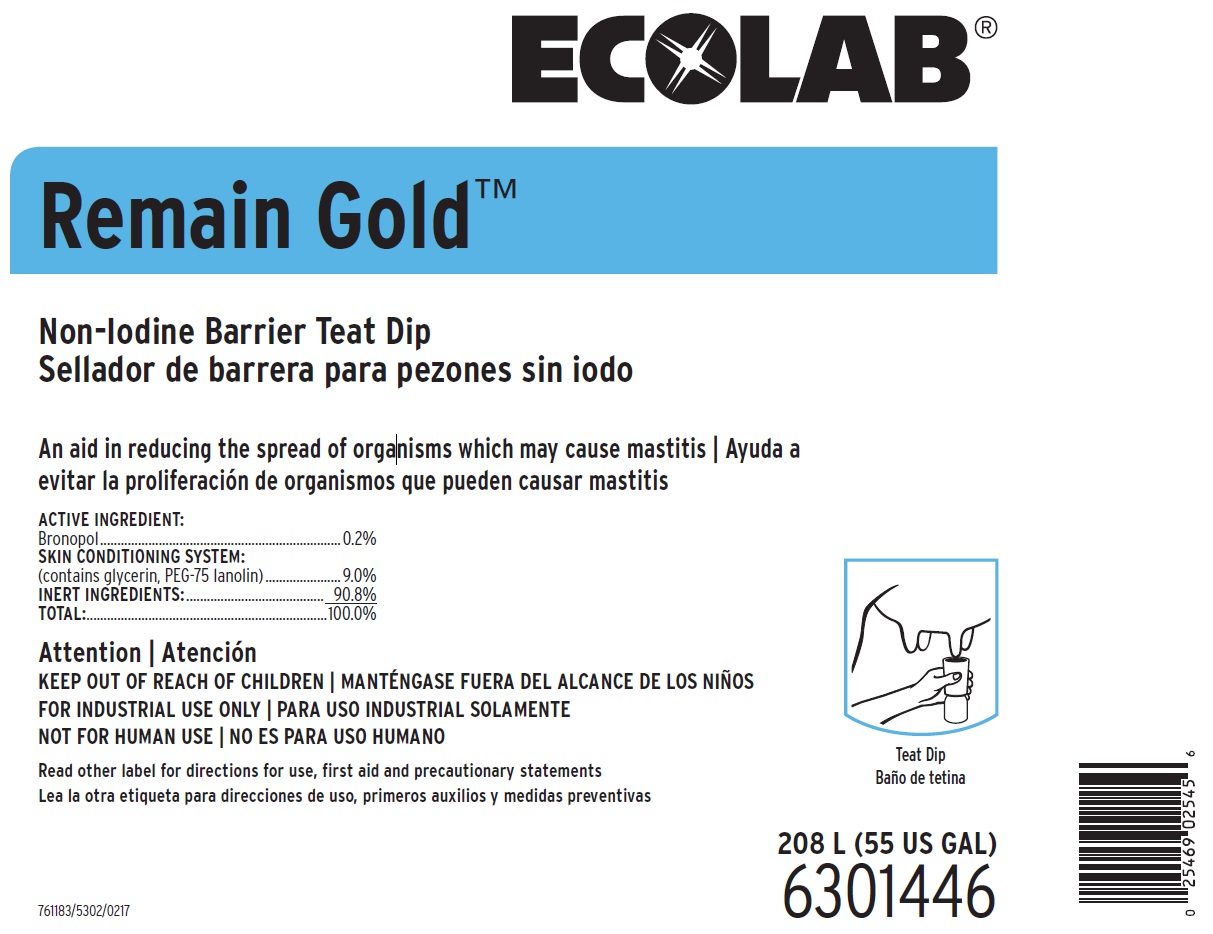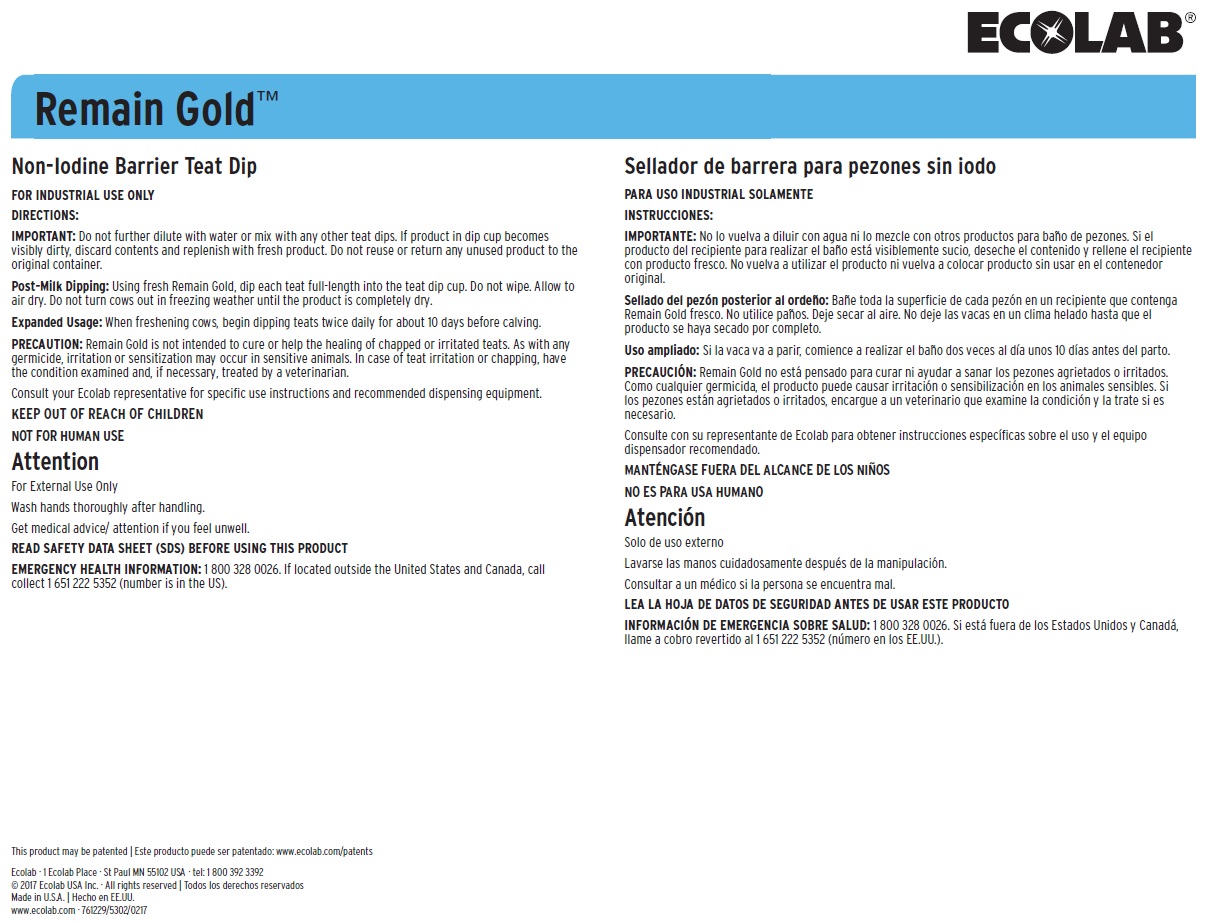 DRUG LABEL: Remain Gold
NDC: 47593-539 | Form: SOLUTION
Manufacturer: Ecolab Inc.
Category: animal | Type: OTC ANIMAL DRUG LABEL
Date: 20250925

ACTIVE INGREDIENTS: BRONOPOL 2 mg/1 mL
INACTIVE INGREDIENTS: GLYCERIN; LANOLIN; WATER

SAFE HANDLING WARNING

Attention

KEEP OUT OF REACH OF CHILDREN

FOR INDUSTRIAL USE ONLY

NOT FOR HUMAN USE

Read other label for directions for use, first aid and precautionary statements

Attention

For External Use Only

Wash hands thoroughly after handling.

Get medical advice/ attention if you feel unwell.

DIRECTIONS:

IMPORTANT: Do not further dilute with water or mix with any other teat dips. If product in dip cup becomes visibly dirty, discard contents and replenish with fresh product. Do not reuse or return any unused product to the original container.

Post-Milk Dipping: Using fresh Remain Gold, dip each teat full-length into the teat dip cup. Do not wipe. Allow to air dry. Do not turn cows out in freezing weather until the product is completely dry.

Expanded Usage: When freshening cows, begin dipping teats twice daily for about 10 days before calving.

PRECAUTION: Remain Gold is not intended to cure or help the healing of chapped or irritated teats. As with any germicide, irritation or sensitization may occur in sensitive animals. In case of teat irritation or chapping, have the condition examined and, if necessary, treated by a veterinarian.

Consult your Ecolab representative for specific use instructions and recommended dispensing equipment.

OTHER SAFETY INFORMATION

READ SAFETY DATA SHEET (SDS) BEFORE USING THIS PRODUCT

EMERGENCY HEALTH INFORMATION: 1 800 328 0026. If located outside the United States and Canada, call collect 1 651 222 5352 (number is in the US).

PACKAGE LABEL

ECOLAB

Remain Gold™

Non-Iodine Barrier Teat Dip

An aid in reducing the spread of organisms which may cause mastitis

ACTIVE INGREDIENT:

Bronopol ......................................................................0.2%

SKIN CONDITIONING SYSTEM:

(contains glycerin, PEG-75 lanolin) ......................9.0%

INERT INGREDIENTS: ........................................ 90.8%

TOTAL:......................................................................100.0%

18.9 L (5 US GAL)

6301444

This product may be patented

Ecolab · 1 Ecolab Place · St Paul MN 55102 USA · tel: 1 800 392 3392

© 2017 Ecolab USA Inc. · All rights reserved

Made in U.S.A.

www.ecolab.com · 761229/5302/0217